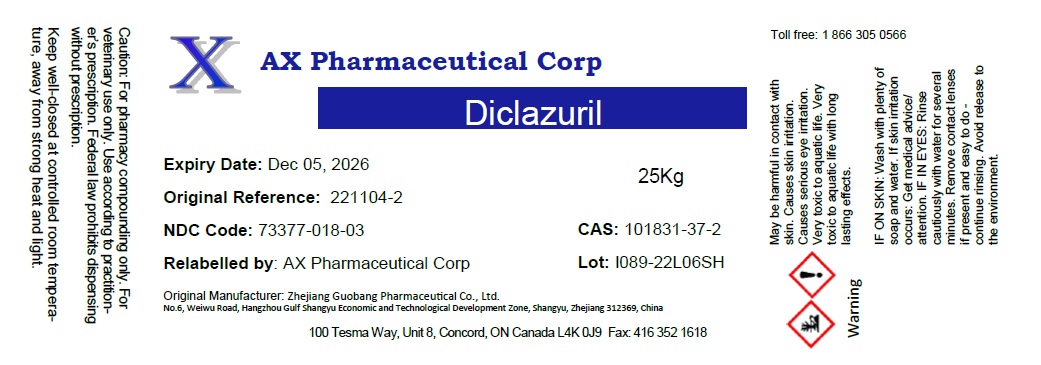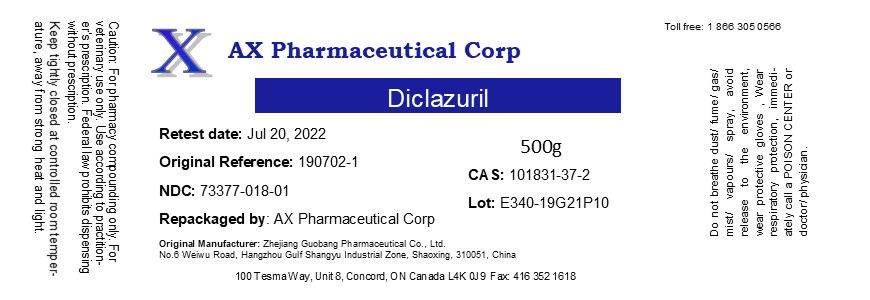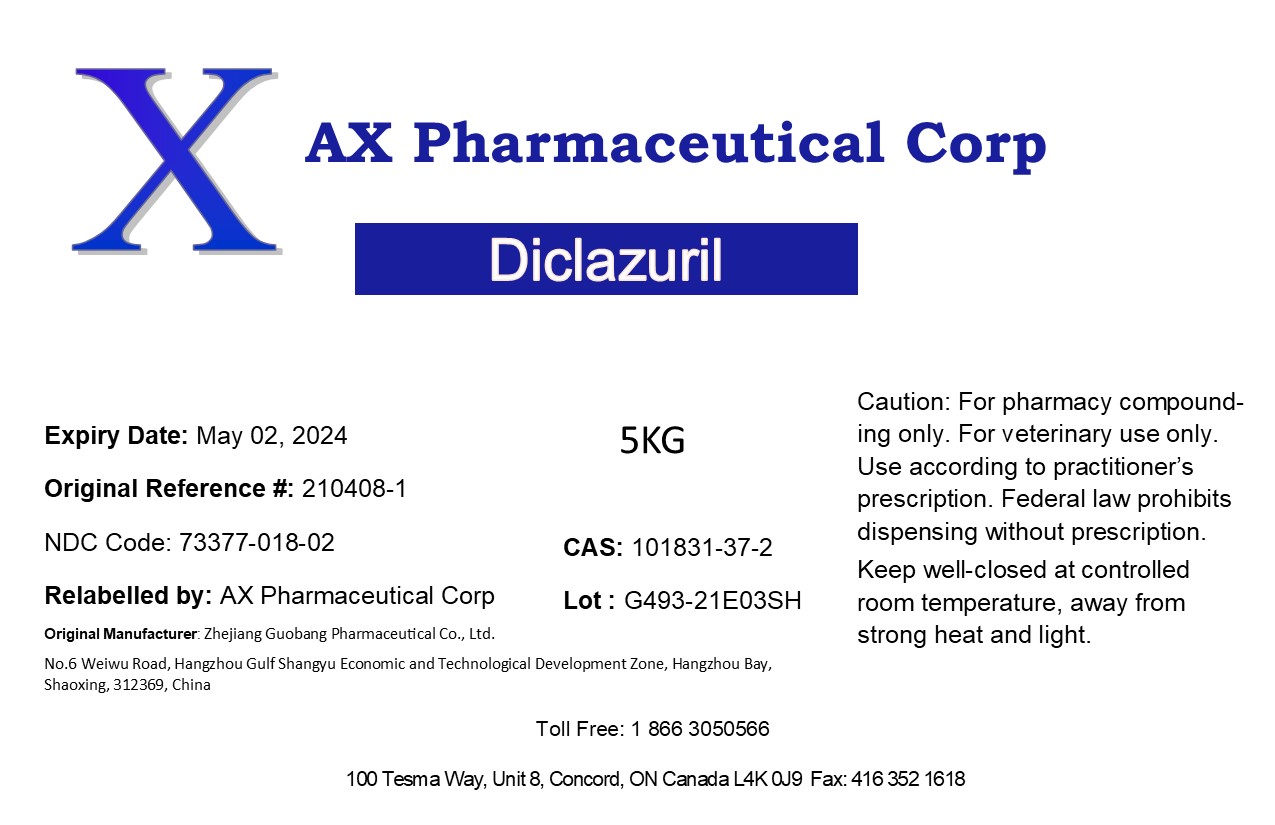 DRUG LABEL: Diclazuril
NDC: 73377-018 | Form: POWDER
Manufacturer: AX Pharmaceutical Corp
Category: other | Type: BULK INGREDIENT - ANIMAL DRUG
Date: 20241021

ACTIVE INGREDIENTS: DICLAZURIL 1 g/1 g

Diclazuril